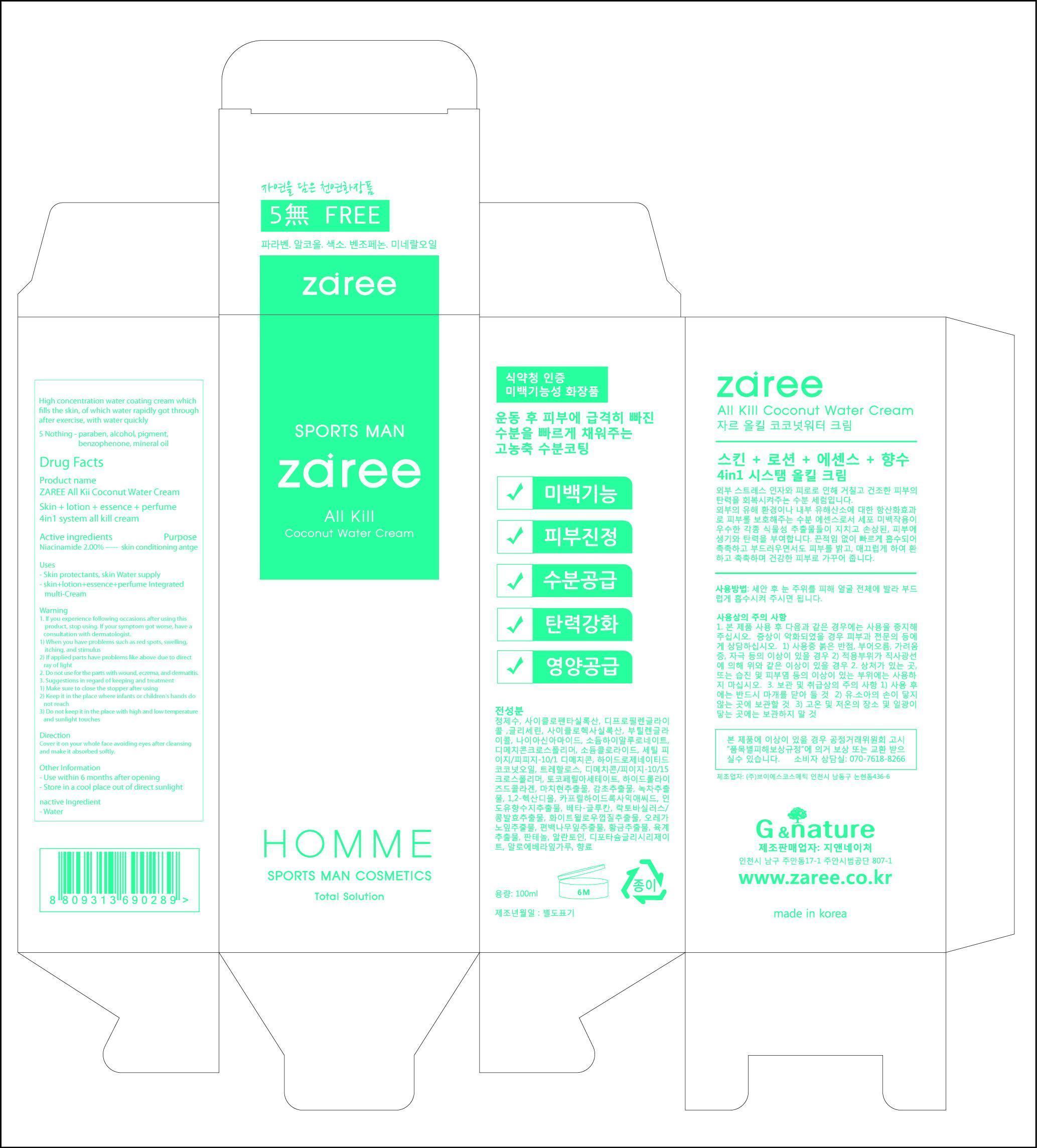 DRUG LABEL: ZAREE All Kii Coconut Water
NDC: 58690-1001 | Form: CREAM
Manufacturer: G & NATURE Co., Ltd.
Category: otc | Type: HUMAN OTC DRUG LABEL
Date: 20130527

ACTIVE INGREDIENTS: Allantoin 0.02 mg/1 mL
INACTIVE INGREDIENTS: WATER; GLYCERIN; .ALPHA.-TOCOPHEROL ACETATE; SODIUM CHLORIDE; DIMETHICONE; COCONUT OIL; ALOE VERA LEAF; NIACINAMIDE

Drug Facts

ACTIVE INGREDIENT

allantoin

INACTIVE INGREDIENT

water, niacinamide, glycerine, butylene glycol, dimethicone, tocopheryl acetate, green tea extract, panthenol, aloe vera extract

PURPOSE

skin protentants

keep out of reach of the children

INDICATIONS AND USAGE

Cover it on your whole face avoiding eyes after cleansing and make it absorbed softly.

WARNINGS

1. If you experience following occasions after using this product, stop using. If your symptom got worse, have a consultation with dermatologist.
1) When you have problems such as red spots, swelling, itching, and stimulus
2) If applied parts have problems like above due to direct ray of light
2. Do not use for the parts with wound, eczema, and dermatitis.
3. Suggestions in regard of keeping and treatment
1) Make sure to close the stopper after using
2) Keep it in the place where infants or children's hands do not reach
3) Do not keep it in the place with high and low temperature and sunlight touches

DOSAGE AND ADMINISTRATION

for topical use only